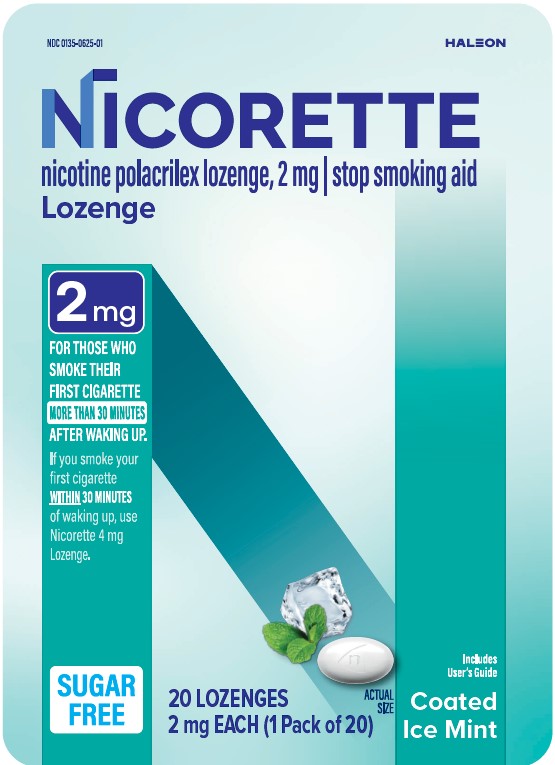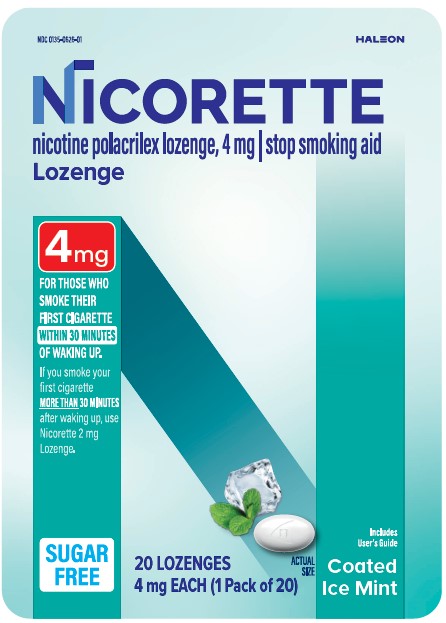 DRUG LABEL: NICORETTE
NDC: 0135-0625 | Form: LOZENGE
Manufacturer: Haleon US Holdings LLC
Category: otc | Type: HUMAN OTC DRUG LABEL
Date: 20250604

ACTIVE INGREDIENTS: NICOTINE 2 mg/1 1
INACTIVE INGREDIENTS: POLACRILIN; ACESULFAME POTASSIUM; HYPROMELLOSE, UNSPECIFIED; MAGNESIUM STEARATE; MANNITOL; MICROCRYSTALLINE CELLULOSE; POLYSORBATE 80; POTASSIUM; ALUMINUM SILICATE; SODIUM CARBONATE; SUCRALOSE; TITANIUM DIOXIDE; XANTHAN GUM

Drug Facts

Active ingredient (in each lozenge) (2 mg)

Nicotine polacrilex, 2 mg

Active ingredient (in each lozenge) (4 mg)

Nicotine polacrilex, 4 mg

Purpose

Stop smoking aid

Use

- reduces withdrawal symptoms, including nicotine craving, associated with quitting smoking

Warnings

If you are pregnant or breast-feeding, only use this medicine on the advice of your health care provider.

Smoking can seriously harm your child. Try to stop smoking without using any nicotine replacement medicine. This medicine is believed to be safer than smoking. However, the risks to your child from this medicine are not fully known.

Ask a doctor before use if you have

- heart disease, recent heart attack, or irregular heartbeat. Nicotine can increase your heart rate.
- high blood pressure not controlled with medication. Nicotine can increase your blood pressure.
- stomach ulcer or diabetes
- history of seizures

Ask a doctor or pharmacist before use if you are

- using a non-nicotine stop smoking drug
- taking prescription medicine for depression or asthma. Your prescription dose may need to be adjusted.

Stop use and ask a doctor if

- mouth problems occur
- persistent indigestion or severe sore throat occurs
- irregular heartbeat or palpitations occur
- you get symptoms of nicotine overdose such as nausea, vomiting, dizziness, diarrhea, weakness and rapid heartbeat
- you have symptoms of an allergic reaction (such as difficulty breathing or rash)

Keep out of reach of children and pets.

Nicotine lozenges may have enough nicotine to make children and pets sick. If you need to remove the lozenge, wrap it in paper and throw away in the trash. In case of overdose, get medical help or contact a Poison Control Center right away.

Directions (2 mg)

- if you are under 18 years of age, ask a doctor before use. No studies have been done to show if this product will work for you.
- before using this product, read the enclosed User’s Guide for complete directions and other important information
- begin using the lozenge on your quit day
- if you smoke your first cigarette within 30 minutes of waking up,use 4 mg nicotine lozenge
- if you smoke your first cigarette more than 30 minutes after waking up,use 2 mg nicotine lozenge according to the following 12 week schedule:

Weeks 1 to 6 | Weeks 7 to 9 | Weeks 10 to 12
1 lozenge every; 1 to 2 hours | 1 lozenge every; 2 to 4 hours | 1 lozenge every; 4 to 8 hours

- nicotine lozenge is a medicine and must be used a certain way to get the best results
- place the lozenge in your mouth and allow the lozenge to slowly dissolve. Minimize swallowing. Do not chew or swallow lozenge.
- you may feel a warm or tingling sensation
- occasionally move the lozenge from one side of your mouth to the other until completely dissolved
- do not eat or drink 15 minutes before using or while the lozenge is in your mouth
- to improve your chances of quitting, use at least 9 lozenges per day for the first 6 weeks
- do not use more than one lozenge at a time or continuously use one lozenge after another since this may cause you hiccups, heartburn, nausea or other side effects
- do not use more than 5 lozenges in 6 hours. Do not use more than 20 lozenges per day.
- it is important to complete treatment. If you feel you need to use the lozenge for a longer period to keep from smoking, talk to your health care provider.

Directions (4 mg)

- if you are under 18 years of age, ask a doctor before use. No studies have been done to show if this product will work for you.
- before using this product, read the enclosed User’s Guide for complete directions and other important information
- begin using the lozenge on your quit day
- if you smoke your first cigarette more than 30 minutes after waking up,use 2 mg nicotine lozenge
- if you smoke your first cigarette within 30 minutes of waking up,use 4 mg nicotine lozenge according to the following 12 week schedule:

Weeks 1 to 6 | Weeks 7 to 9 | Weeks 10 to 12
1 lozenge every; 1 to 2 hours | 1 lozenge every; 2 to 4 hours | 1 lozenge every; 4 to 8 hours

- nicotine lozenge is a medicine and must be used a certain way to get the best results
- place the lozenge in your mouth and allow the lozenge to slowly dissolve. Minimize swallowing. Do not chew or swallow lozenge.
- you may feel a warm or tingling sensation
- occasionally move the lozenge from one side of your mouth to the other until completely dissolved
- do not eat or drink 15 minutes before using or while the lozenge is in your mouth
- to improve your chances of quitting, use at least 9 lozenges per day for the first 6 weeks
- do not use more than one lozenge at a time or continuously use one lozenge after another since this may cause you hiccups, heartburn, nausea or other side effects
- do not use more than 5 lozenges in 6 hours. Do not use more than 20 lozenges per day.
- it is important to complete treatment. If you feel you need to use the lozenge for a longer period to keep from smoking, talk to your health care provider.

Other information

- store at 20 - 25°C (68 - 77°F)
- store in the original container

Inactive ingredients

acesulfame potassium, flavors, hypromellose, magnesium stearate, mannitol, microcrystalline cellulose, polysorbate 80, potassium aluminum silicate, sodium carbonate anhydrous, sucralose, titanium dioxide, xanthan gum

Questions or comments?

call toll-free 1-888-569-1743

Additional Information

- not for sale to those under 18 years of age
- proof of age required
- not for sale in vending machines or from any source
- where proof of age cannot be verified

TAMPER EVIDENT FEATURE:The lozenge container is protected in a clear plastic shell, sealed to a printed card.

Do not use if the printed card or plastic shell is torn or broken, or if there is any evidence that the printed card was separated from the plastic shell.

Retain this package for complete product information.

Includes Quit Support Program

TO INCREASE YOUR SUCCESS IN QUITTING:

1. You must be motivated to quit.
2. Use Enough - Use at least 9 Nicorette Lozenges per day during the first six weeks.
3. Use Long Enough - Use Nicorette for the full 12 weeks.
4. Use With a Support Program as directed in the enclosed User’s Guide.

For more information and for a FREE individualized stop smoking program, please visit www.Nicorette.comor see inside for more details.

TO OPEN

PUSH

LIFT

TO CLOSE

Push Cap Closed until you hear a CLICK to ensure child resistance

CLICK

Distributed By:

Haleon

Warren, NJ 07059

Made in the Switzerland

Trademarks are owned by or licensed to the Haleon group of companies.

©2023 Haleon group of companies or its licensor.

Principal Display Panel

NDC 0135-0625-01

HALEON

NICORETTE

nicotine polacrilex lozenge, 2 mg ׀ stop smoking aid

Lozenge

2 mg

FOR THOSE WHO SMOKE THEIR FIRST CIGARETTE MORE THAN 30 MINUTES AFTER WAKING UP.

If you smoke your first cigarette WITHIN30 MINUTES of waking up, use Nicorette 4 mg Lozenge.

SUGAR FREE

20 LOZENGES, 2 mg EACH (1 Pack of 20)

Includes User’s Guide

Coated Ice Mint

216965

Principal Display Panel

NDC 0135-0626-01

HALEON

NICORETTE

nicotine polacrilex lozenge, 4 mg ׀ stop smoking aid

Lozenge

4 mg

FOR THOSE WHO SMOKE THEIR FIRST CIGARETTE WITHIN 30 MINUTES OF WAKING UP.

If you smoke your first cigarette MORE THAN30 MINUTES after waking up, use Nicorette 2 mg Lozenge.

SUGAR FREE

20 LOZENGES, 4 mg EACH (1 Pack of 20)

Includes User’s Guide

Coated Ice Mint

216969